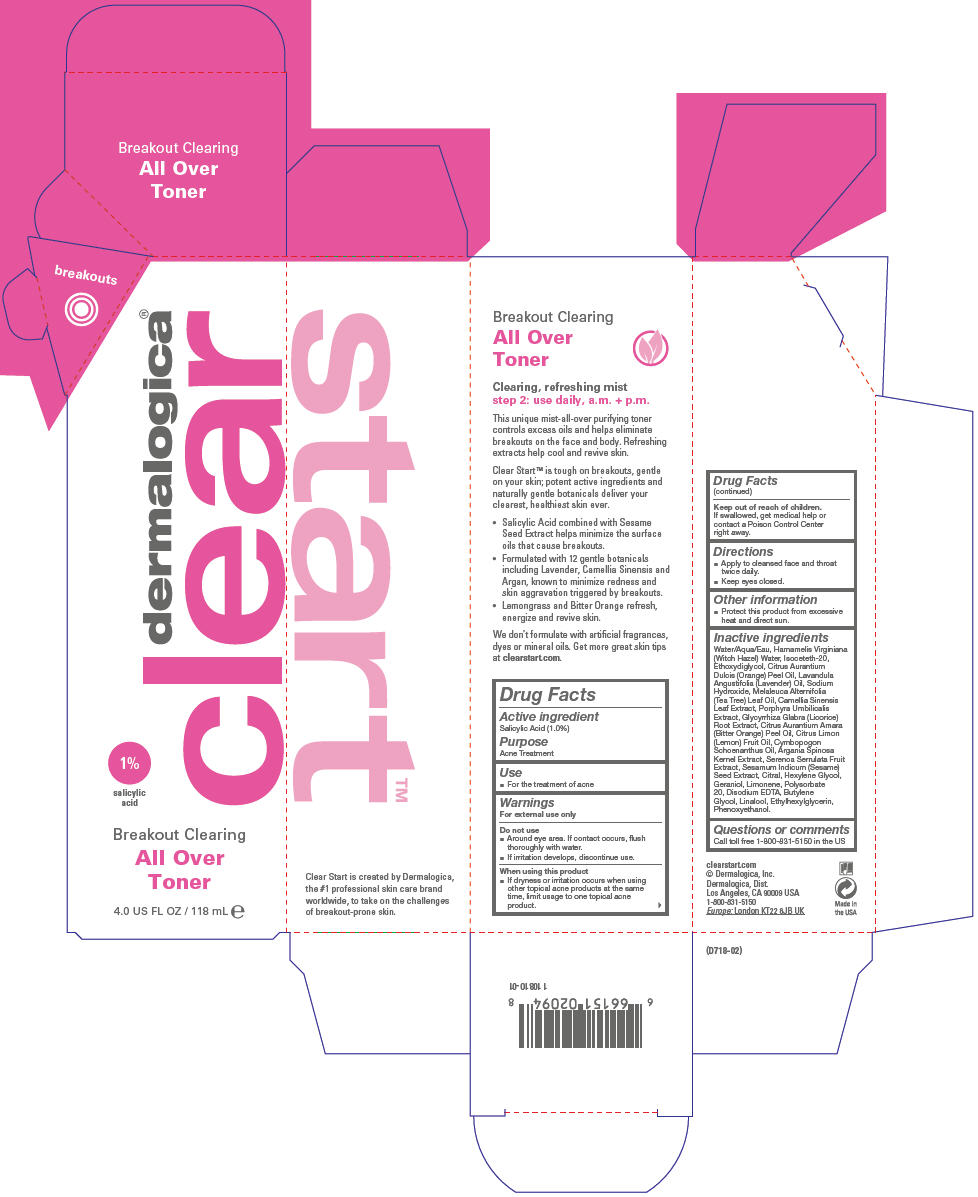 DRUG LABEL: Breakout Clearing All Over Toner
NDC: 68479-312 | Form: LIQUID
Manufacturer: Dermalogica, Inc.
Category: otc | Type: HUMAN OTC DRUG LABEL
Date: 20140205

ACTIVE INGREDIENTS: Salicylic Acid 10 mg/1 mL
INACTIVE INGREDIENTS: Water; Hamamelis Virginiana Top Water; Isoceteth-20; Diethylene Glycol Monoethyl Ether; Hexylene Glycol; Orange Oil; Lavender Oil; Sodium Hydroxide; Tea Tree Oil; Green Tea Leaf; Porphyra Umbilicalis; .Beta.-Sitosterol; Glycyrrhiza Glabra; Bitter Orange Oil; Citrus Limon Fruit Oil; Cymbopogon Schoenanthus Oil; Argania Spinosa Seed; Saw Palmetto; Sesame Seed; Polysorbate 20; Edetate Disodium; Butylene Glycol; Ethylhexylglycerin; Phenoxyethanol

Breakout Clearing All Over Toner

Drug Facts

Active ingredient

Salicylic Acid (1.0%)

Purpose

Acne Treatment

Use

- For the treatment of acne

Warnings

For external use only

Do not use

- Around eye area. If contact occurs, flush thoroughly with water.
- If irritation develops, discontinue use.

When using this product

- If dryness or irritation occurs when using other topical acne products at the same time, limit usage to one topical acne product.

Keep out of reach of children.

If swallowed, get medical help or contact a Poison Control Center right away.

Directions

- Apply to cleansed face and throat twice daily.
- Keep eyes closed.

Other information

- Protect this product from excessive heat and direct sun.

Inactive ingredients

Water/Aqua/Eau, Hamamelis Virginiana (Witch Hazel) Water, Isoceteth-20, Ethoxydiglycol, Citrus Aurantium Dulcis (Orange) Peel Oil, Lavandula Angustifolia (Lavender) Oil, Sodium Hydroxide, Melaleuca Alternifolia (Tea Tree) Leaf Oil, Camellia Sinensis Leaf Extract, Porphyra Umbilicalis Extract, Glycyrrhiza Glabra (Licorice) Root Extract, Citrus Aurantium Amara (Bitter Orange) Peel Oil, Citrus Limon (Lemon) Fruit Oil, Cymbopogon Schoenanthus Oil, Argania Spinosa Kernel Extract, Serenoa Serrulata Fruit Extract, Sesamum Indicum (Sesame) Seed Extract, Citral, Hexylene Glycol, Geraniol, Limonene, Polysorbate 20, Disodium EDTA, Butylene Glycol, Linalool, Ethylhexylglycerin, Phenoxyethanol.

Questions or comments

Call toll free 1-800-831-5150 in the US

PRINCIPAL DISPLAY PANEL - 118 mL Bottle Carton

dermalogica®
clear

1%
salicylic
acid

Breakout Clearing
All Over
Toner

4.0 US FL OZ / 118 mL e